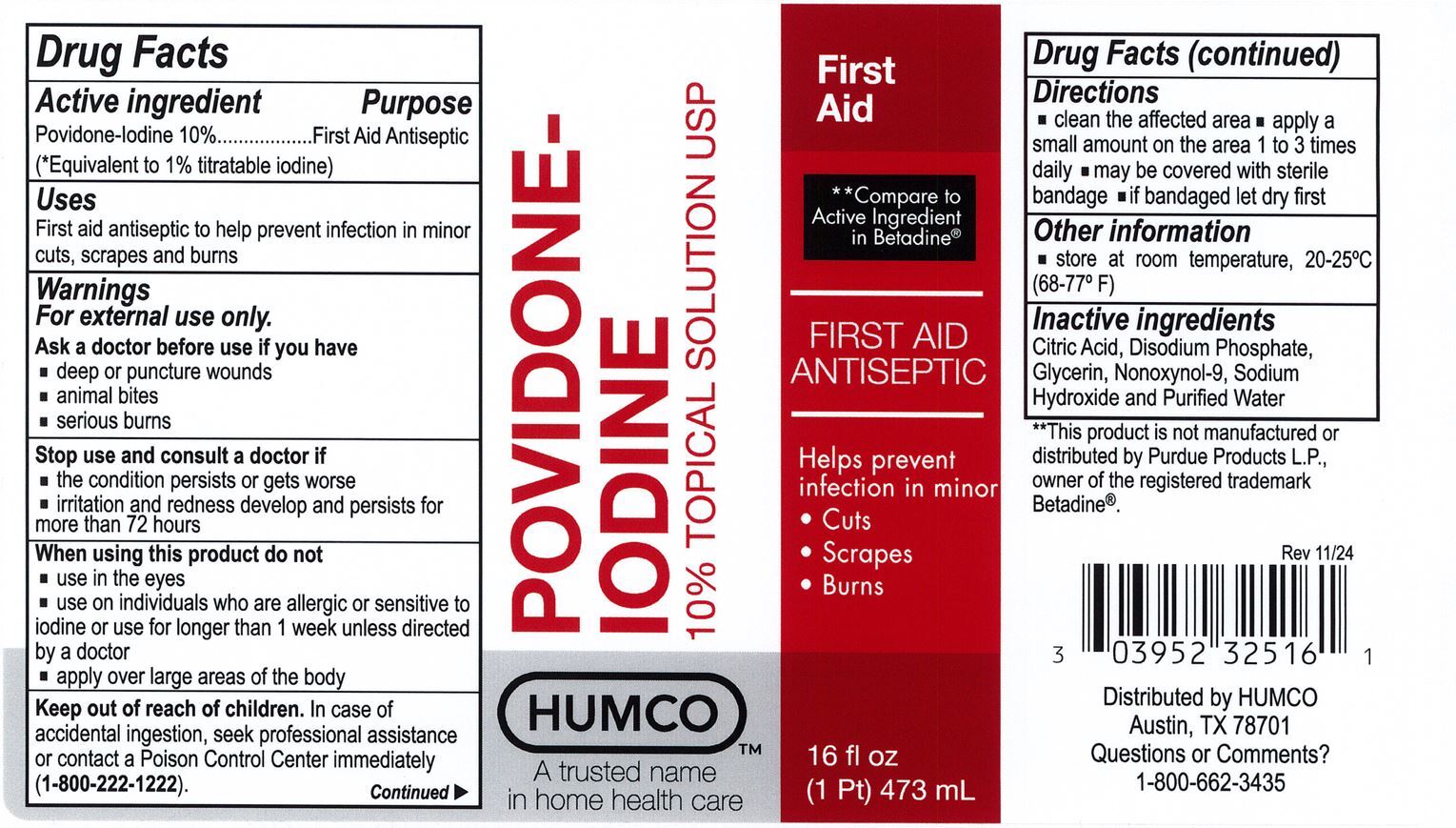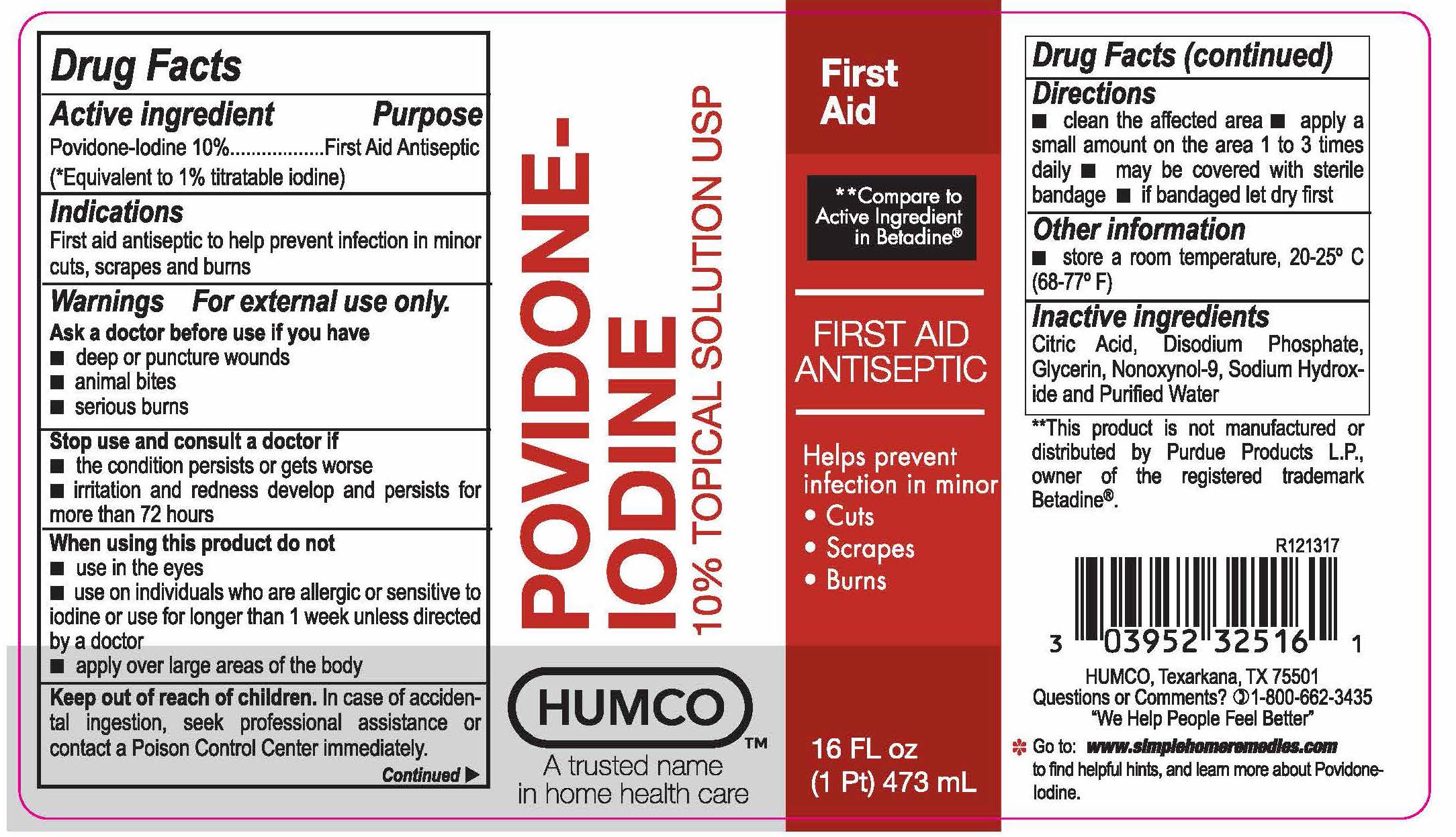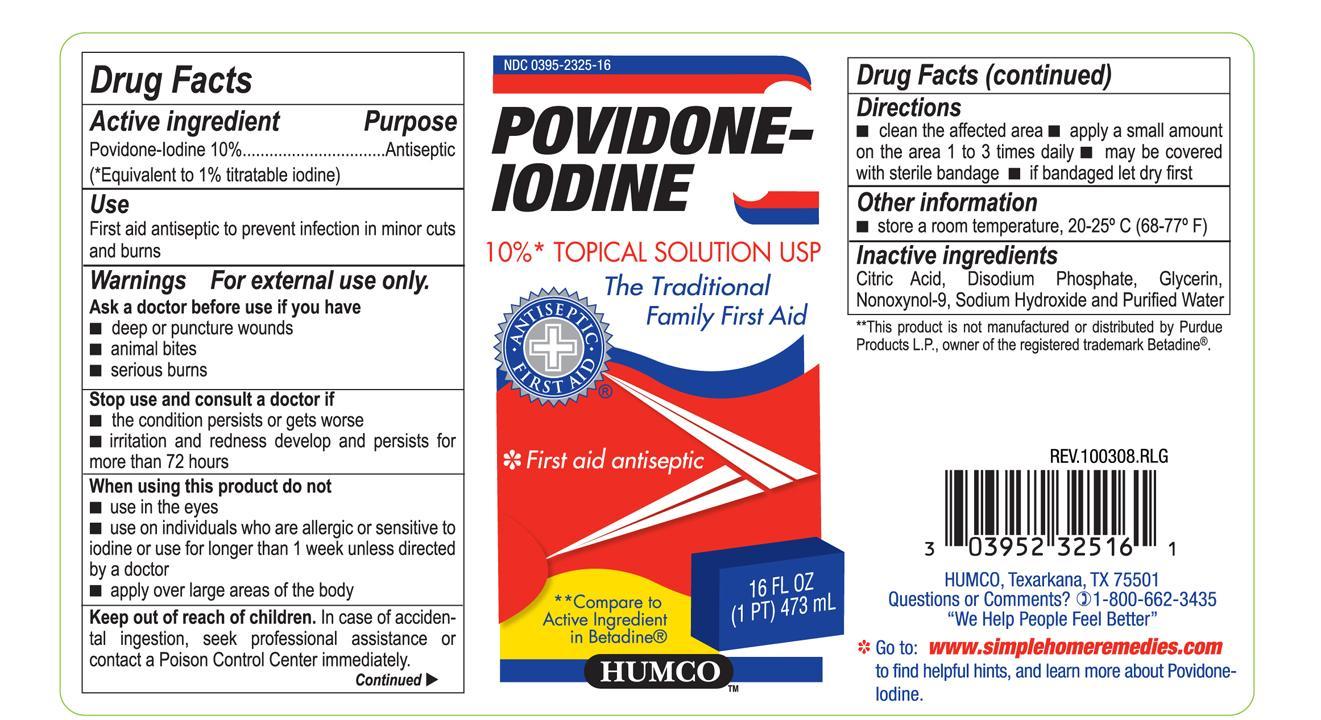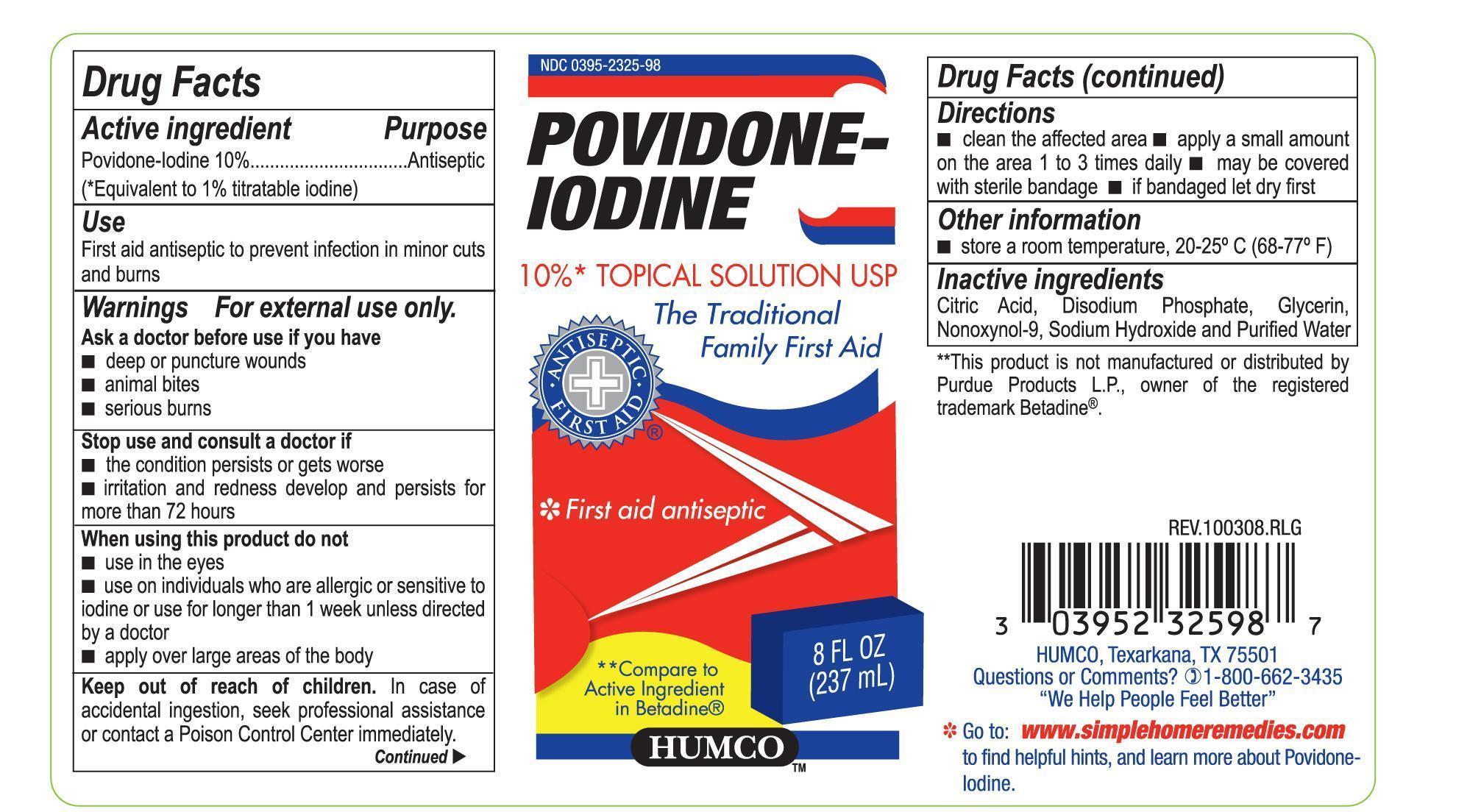 DRUG LABEL: Humco Povidone Iodine
NDC: 0395-2325 | Form: LIQUID
Manufacturer: Humco Holding Group, Inc.
Category: otc | Type: HUMAN OTC DRUG LABEL
Date: 20241218

ACTIVE INGREDIENTS: POVIDONE-IODINE 100 mg/1 mL
INACTIVE INGREDIENTS: ANHYDROUS CITRIC ACID; GLYCERIN; NONOXYNOL-9; SODIUM HYDROXIDE; WATER

Humco Povidone Iodine

Drug Facts

Active Ingredient

Povidone-Iodine 10%

(Equivalent to 1% titrable iodine)

Purpose

Antiseptic

Use

First aid antiseptic to prevent infection in minor cuts and burns.

Warnings

For External Use Only

Ask a doctor before use if you have

- deep punture wounds
- animal bites
- serious burns

Stop use and consult a doctor if

- the condition persists or gets worse
- irritation and redness develop and persits for more than 72 hours

When using this product do not

- use in eyes
- use on individuals who are allergic or sensitive to iodine or use for longer thn 1 week unless directed by a doctor
- apply over large areas of the body

Keep out of reach of children.

In case of accidental ingestion, seek professional assistance or contact a Poison Control Center immediately.

Directions

Clean the affected area. Apply a small amount on the area 1 to 3 times daily. May be covered with sterile bandage. If badaged, let it dry first.

Other information

store at room temperature, 20-25C (68-77F)

Inactive Ingredients

Citric Acid, Disodium Phosphate, Glycerin, nonoxynol-9. Sodium Hydroxide and Purified Water.

Principal Display Panel

Label 8 fl oz

Principal Display Panel

Label 16 fl oz